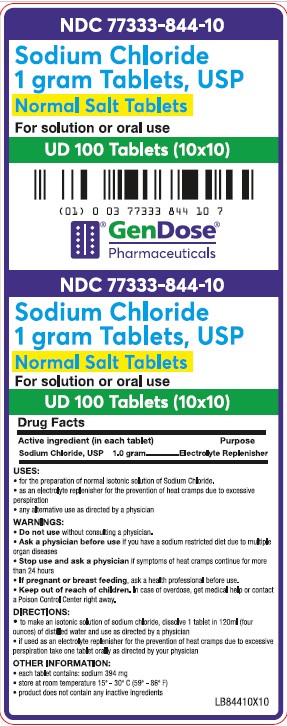 DRUG LABEL: SODIUM CHLORIDE

NDC: 77333-844 | Form: TABLET
Manufacturer: Gendose Pharmaceuticals, LLC
Category: otc | Type: HUMAN OTC DRUG LABEL
Date: 20250702

ACTIVE INGREDIENTS: SODIUM CHLORIDE 1 g/1 1

GENDOSE - SODIUM CHLORIDE 1 GRAM TABLETS, USP (77333-844)

ACTIVE INGREDIENT (IN EACH TABLET)

SODIUM CHLORIDE, USP 1.0 GRAM

PURPOSE

ELECTROLYTE REPLENISHER

USES

- FOR THE PREPARATION OF NORMAL ISOTONIC SOLUTION OF SODIUM CHLORIDE.
- AS AN ELECTROLYTE REPLENISHER FOR THE PREVENTION OF HEAT CRAMPS DUE TO EXCESSIVE PERSPIRATION.
- ANY ALTERNATIVE USE AS DIRECTED BY A PHYSICIAN.

WARNINGS

- DO NOT USE WITHOUT CONSULTING A PHYSICIAN.
- ASK A PHYSICIAN BEFORE USE IF YOU HAVE A SODIUM RESTRICTED DIET DUE TO MULTIPLE ORGAN DISEASES.
- STOP USE AND ASK A PHYSICIAN IF SYMPTOMS OF HEAT CRAMPS CONTINUE FOR MORE THAN 24 HOURS.
- IF PREGNANT OR BREAST FEEDING, ASK A HEALTH PROFESSIONAL BEFORE USE.

- KEEP OUT OF REACH OF CHILDREN. IN CASE OF OVERDOSE, GET MEDICAL HELP OR CONTACT A POISON CONTROL CENTER RIGHT AWAY.

DIRECTIONS

- TO MAKE AN ISOTONIC SOLUTION OF SODIUM CHLORIDE, DISSOLVE 1 TABLET IN 120 ML (FOUR OUNCES) OF DISTILLED WATER AND USE AS DIRECTED BY A PHYSICIAN.
- IF USED AS AN ELECTROLYTE REPLENISHER FOR THE PREVENTION OF HEAT CRAMPS DUE TO EXCESSIVE PERSPIRATION TAKE ONE TABLET ORALLY AS DIRECTED BY YOUR PHYSICIAN.

INACTIVE INGREDIENTS

NONE

OTHER INFORMATION

- EACH TABLET CONTAINS: SODIUM 394 MG
- STORE AT ROOM TEMPERATURE 15° - 30°C (59° - 86°F)
- PRODUCT DOES NOT CONTAINS ANY INACTIVE INGREDIENTS.